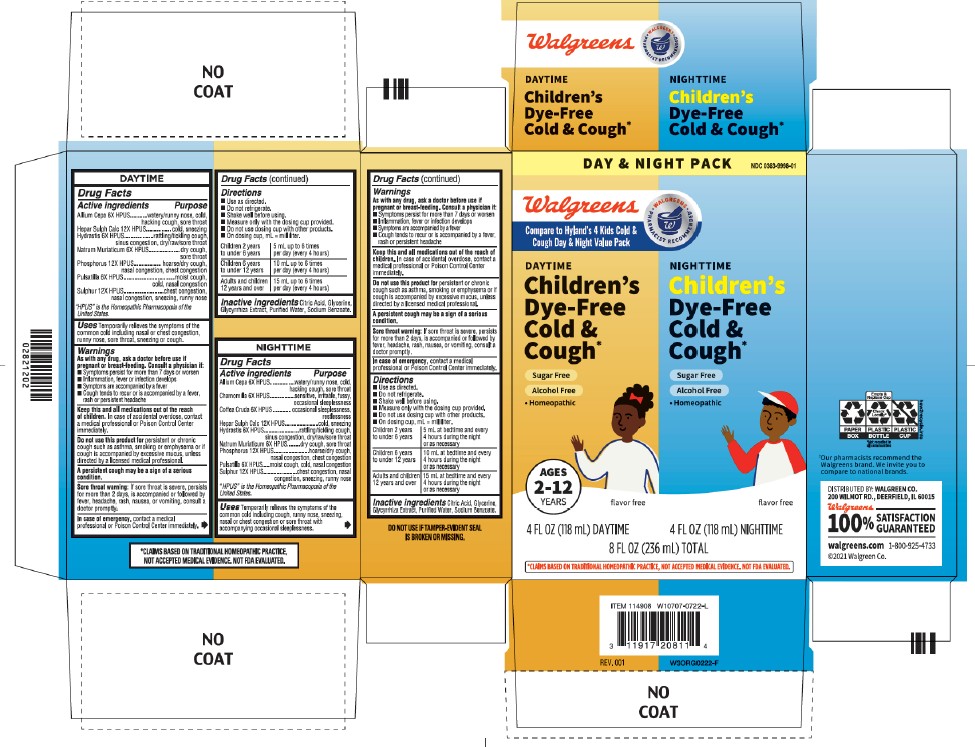 DRUG LABEL: Childrens Cold and Cough Day and Night Value Pack
NDC: 0363-9998 | Form: KIT | Route: ORAL
Manufacturer: Walgreen Company
Category: homeopathic | Type: HUMAN OTC DRUG LABEL
Date: 20251219

ACTIVE INGREDIENTS: SODIUM CHLORIDE 6 [hp_X]/1 mL; CALCIUM SULFIDE 12 [hp_X]/1 mL; SULFUR 12 [hp_X]/1 mL; PHOSPHORUS 12 [hp_X]/1 mL; GOLDENSEAL 6 [hp_X]/1 mL; ONION 6 [hp_X]/1 mL; ANEMONE PULSATILLA 6 [hp_X]/1 mL; ARABICA COFFEE BEAN 6 [hp_X]/1 mL; ONION 6 [hp_X]/1 mL; CALCIUM SULFIDE 12 [hp_X]/1 mL; PHOSPHORUS 12 [hp_X]/1 mL; SODIUM CHLORIDE 6 [hp_X]/1 mL; ANEMONE PULSATILLA 6 [hp_X]/1 mL; MATRICARIA CHAMOMILLA 6 [hp_X]/1 mL; GOLDENSEAL 6 [hp_X]/1 mL; SULFUR 12 [hp_X]/1 mL
INACTIVE INGREDIENTS: WATER; GLYCERIN; CITRIC ACID MONOHYDRATE; SODIUM BENZOATE; GLYCYRRHIZA GLABRA; SODIUM BENZOATE; GLYCYRRHIZA GLABRA; GLYCERIN; WATER; CITRIC ACID MONOHYDRATE

Walgreen's Children's Cold & Cough Day & Night Pack

Purpose

Temporarily relieves the symptoms of the common cold including cough, runny nose, sneezing, nasal or chest congestion or sore throat with accompanying occasional sleeplessness.

DAYTIME

Drug Facts

Active ingredients | Purpose
Allium Cepa 6X HPUS | watery/runny nose, cold, hacking cough, sore throat
Hepar Sulph Calc 12X HPUS | cold, sneezing
Hydrastis 6X HPUS | rattling/tickling cough, sinus congestion, dry/raw/sore throat
Natrum Muriaticum 6X HPUS | dry cough, sore throat
Phosphorus 12X HPUS | hoarse/dry cough, nasal congestion, chest congestion
Pulsatilla 6X HPUS | moist cough, cold, nasal congestion
Sulphur 12X HPUS | chest congestion, nasal congestion, sneezing, runny nose

“HPUS” is the Homeopathic Pharmacopoeia of the United States.

Uses

Temporarily relieves the symptoms of the common cold including nasal or chest congestion, runny nose, sore throat, sneezing or cough.

Warnings

PREGNANCY OR BREAST FEEDING

As with any drug, ask a doctor before use if pregnant or breast-feeding.

Consult a physician if

■ Symptoms persist for more than 7 days or worsen
■ Inflammation, fever or infection develops
■ Symptoms are accompanied by a fever
■ Cough tends to recur or is accompanied by a fever, rash or persistent headache

Keep this and all medications out of the reach of children.

In case of accidental overdose, contact a medical professional or Poison Control Center immediately.

Do not use this product for

Persistent or chronic cough such as asthma, smoking or emphysema or if cough is accompanied by excessive mucus, unless
directed by a licensed medical professional.

Sore throat warning

If sore throat is severe, persists for more than 2 days, is accompanied or followed by fever, headache, rash, nausea, or vomiting, consult a doctor promptly.

In case of emergency

contact a medical professional or Poison Control Center immediately.

Directions

■ Use as directed.
■ Do not refrigerate.
■ Shake well before using.
■ Measure only with the dosing cup provided.
■ Do not use dosing cup with other products.
■ On dosing cup, mL = milliliter.

Children 2 years; to under 6 years | 5 mL up to 6 times; per day (every 4 hours)
Children 6 years; to under 12 years | 10 mL up to 6 times; per day (every 4 hours)
Adults and children; 12 years and over | 15 mL up to 6 times; per day (every 4 hours)

Inactive ingredients

Citric Acid, Glycerine, Glycyrrhiza Extract, Purified Water, Sodium Benzoate.

NIGHTTIME

Drug Facts

Active ingredients | Purpose
Allium Cepa 6X HPUS | watery/runny nose, cold, hacking cough, sore throat
Chamomilla 6X HPUS | sensitive, irritable, fussy, occasional sleeplessness
Coffea Cruda 6X HPUS | occasional sleeplessness, restlessness
Hepar Sulph Calc 12X HPUS | cold, sneezing
Hydrastis 6X HPUS | rattling/tickling cough, sinus congestion, dry/raw/sore throat
Natrum Muriaticum 6X HPUS | dry cough, sore throat
Phosphorus 12X HPUS | hoarse/dry cough, nasal congestion, chest congestion
Pulsatilla 6X HPUS | moist cough, cold, nasal congestion
Sulphur 12X HPUS | chest congestion, nasal congestion, sneezing, runny nose

“HPUS” is the Homeopathic Pharmacopoeia of the United States.

Uses

Temporarily relieves the symptoms of the common cold including cough, runny nose, sneezing, nasal or chest congestion or sore throat with accompanying occasional sleeplessness.

Drug Facts (continued)

Warnings

PREGNANCY OR BREAST FEEDING

As with any drug, ask a doctor before use if pregnant or breast-feeding.

Consult a physician if

■ Symptoms persist for more than 7 days or worsen
■ Inflammation, fever or infection develops
■ Symptoms are accompanied by a fever
■ Cough tends to recur or is accompanied by a fever, rash or persistent headache

Keep this and all medications out of the reach of children.

In case of accidental overdose, contact a medical professional or Poison Control Center
immediately.

Do not use this product for

Persistent or chronic cough such as asthma, smoking or emphysema or if cough is accompanied by excessive mucus, unless
directed by a licensed medical professional.

Sore throat warning

If sore throat is severe, persists for more than 2 days, is accompanied or followed by fever, headache, rash, nausea, or vomiting, consult a doctor promptly.

In case of emergency

Contact a medical professional or Poison Control Center immediately.

Directions

■ Use as directed.
■ Do not refrigerate.
■ Shake well before using.
■ Measure only with the dosing cup provided.
■ Do not use dosing cup with other products.
■ On dosing cup, mL = milliliter.

Children 2 years; to under 6 years | 5 mL at bedtime and every; 4 hours during the night or as necessary
Children 6 years; to under 12 years | 10 mL at bedtime and every; 4 hours during the night; or as necessary
Adults and children; 12 years and over | 15 mL at bedtime and every; 4 hours during the night; or as necessary

Inactive ingredients

Citric Acid, Glycerine, Glycyrrhiza Extract, Purified Water, Sodium Benzoate.

QUESTIONS

walgreens.com 1-800-925-4733

RECENT MAJOR CHANGES

DAYTIME

Dosage and Administration

■ Use as directed.
■ Do not refrigerate.
■ Shake well before using.
■ Measure only with the dosing cup provided.
■ Do not use dosing cup with other products.
■ On dosing cup, mL = milliliter.

NIGHTTIME

Dosage and Administration

■ Use as directed.
■ Do not refrigerate.
■ Shake well before using.

■ Measure only with the dosing cup provided.
■ Do not use dosing cup with other products.
■ On dosing cup, mL = milliliter.

PRINCIPAL DISPLAY PANEL

DAY & NIGHT PACK NDC 0363-9998-01

Walgreens

Compare to Hyland's 4 Kids Cold &

Cough Day & Night Value Pack

WALGREENS PHARMACIST

RECOMMENDED

DAYTIME

Children's

Dye-Free

Cold &

Cough

Sugar Free

Alcohol Free

• Homeopathic

flavor free

4 FL OZ (118 mL) DAYTIME

NIGHTTIME

Children's

Dye-Free

Cold &

Cough

Sugar Free

Alcohol Free

• Homeopathic

flavor free

4 FL OZ (118 mL) NIGHTTIME

8 FL OZ (236 mL) TOTAL

AGES

2-12

YEARS

*CLAIMS BASED ON TRADITIONAL HOMEOPATHIC PRACTICE, NOT ACCEPTED MEDICAL EVIDENCE. NOT FDA EVALUATED.